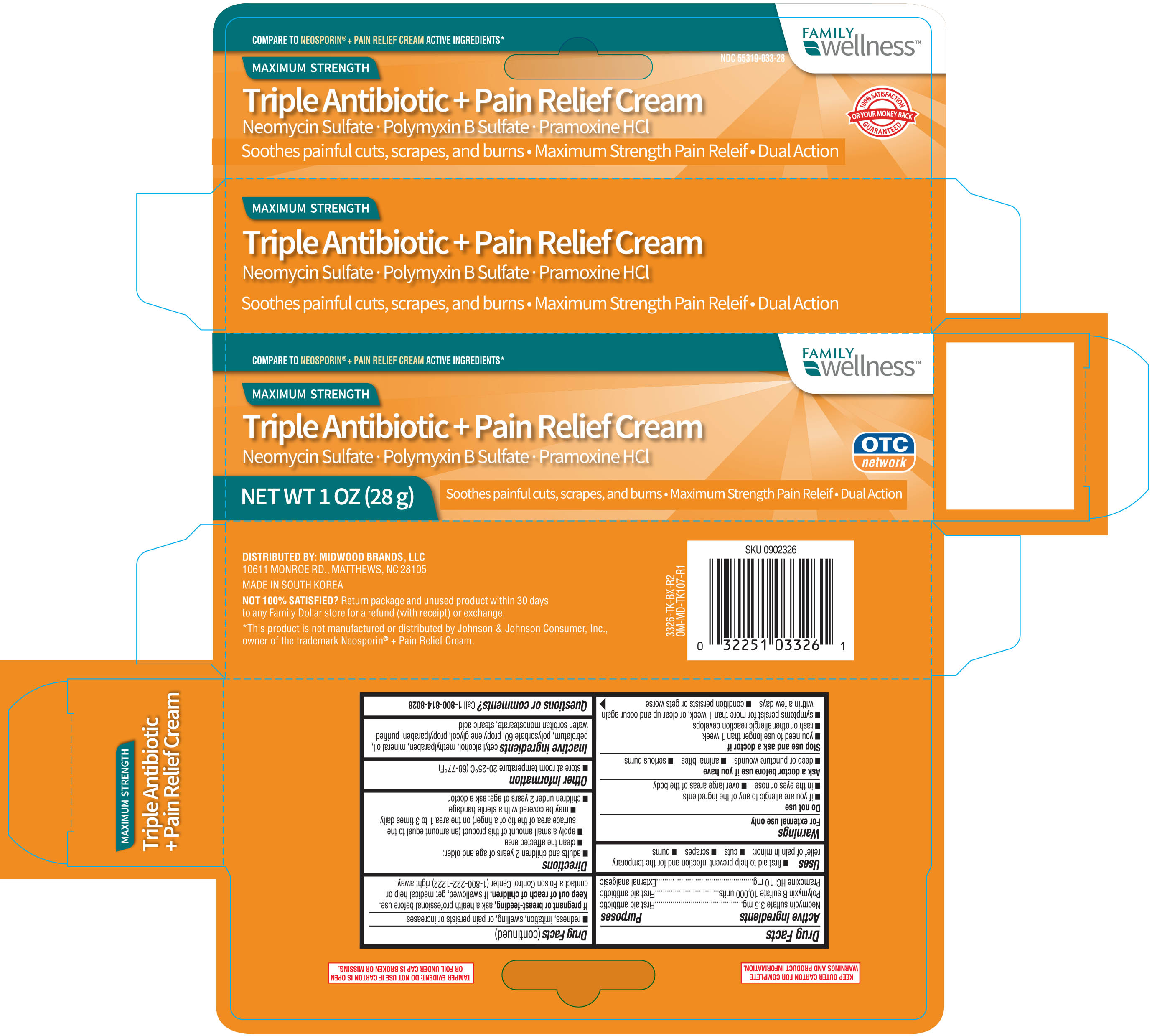 DRUG LABEL: FAMILY WELLNESS TRIPLE ANTIBIOTIC PLUS PAIN RELIEF
NDC: 55319-033 | Form: CREAM
Manufacturer: FAMILY DOLLAR
Category: otc | Type: HUMAN OTC DRUG LABEL
Date: 20190131

ACTIVE INGREDIENTS: NEOMYCIN SULFATE 3.5 mg/1 g; POLYMYXIN B SULFATE 10000 [USP'U]/1 g; PRAMOXINE HYDROCHLORIDE 10 mg/1 g
INACTIVE INGREDIENTS: SORBITAN MONOSTEARATE; WATER; PROPYLPARABEN; CETYL ALCOHOL; PARAFFIN; STEARIC ACID; METHYLPARABEN; PETROLATUM; POLYSORBATE 60

Family Wellness Triple Antibiotic Pain Relief Cream 1 oz. 3326 (2018)

Active ingredients (in each gram) Purpose

Neomycin 3.5mg .......................................................................................................First aid antibiotic

Polymyxin B sulfate 10,000 units ................................................................................First aid antibiotic

Pramoxine hydrochloride 10mg ...................................................................................Pain reliever

Uses

first aid to help prevent infection and for temporary relief of pain or discomfort in minor:

- cuts
- scrapes
- burns

Warnings

For external use only

Do not use

- if you are allergic to any of the ingredients
- in the eyes
- over large areas of the body

Ask a doctor before use if you have

- deep or puncture wounds
- animal bites
- serious burns

Stop use and ask a doctor if

- you need to use longer than 1 week
- condition persists or gets worse
- symptoms persist for more than 1 week or clear up and occur again within a few days
- rash or other allergic reaction develops

Keep out of reach of children. If swallowed, get medical help or contact a Poison Control Center (1-800-222-1222) right away.

INDICATIONS AND USAGE

Directions Adults and children 2 years and older:

- clean affected area
- apply a small amount (equal to the surface area of the tip of a finger) on area 1 to 3 times daily
- may be covered with a sterile bandage

Children under 2 years: ask a doctor

Other information

- Store between 20oC and 25oC (68oF and 77oF)
- Lot No. and Exp. Date: see box or see crimp of tube

Inactive ingredients

cetanol, methylparaben, mineral oil, petrolatum, polysorbate 60, propylene glycol, propylparaben, purified water, sorbitan monostearate, stearic acid

DOSAGE AND ADMINISTRATION

Distributed by:

Midwood Brands, LLC

10811 Monroe Rd.

Matthews, NC 28105

Made in Korea